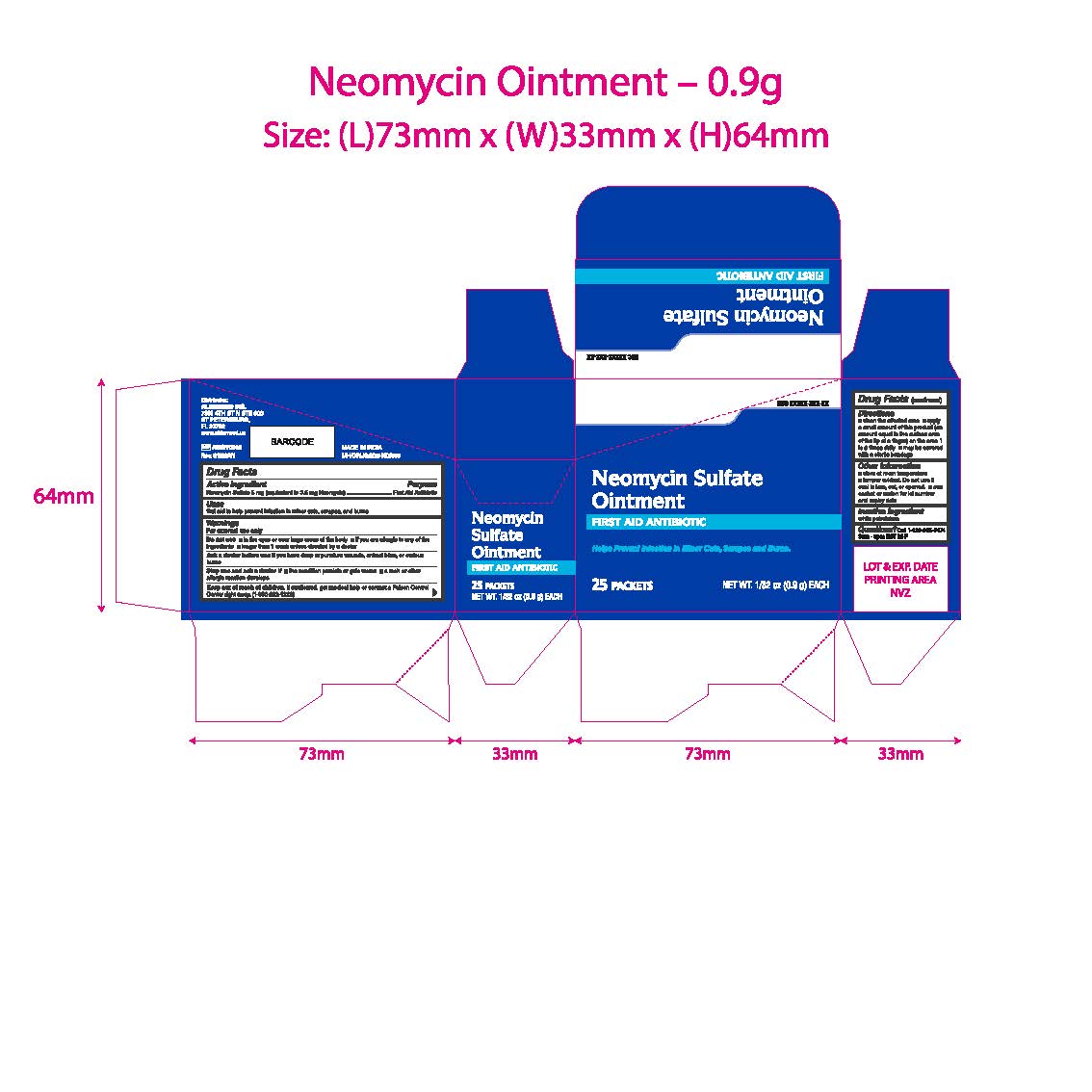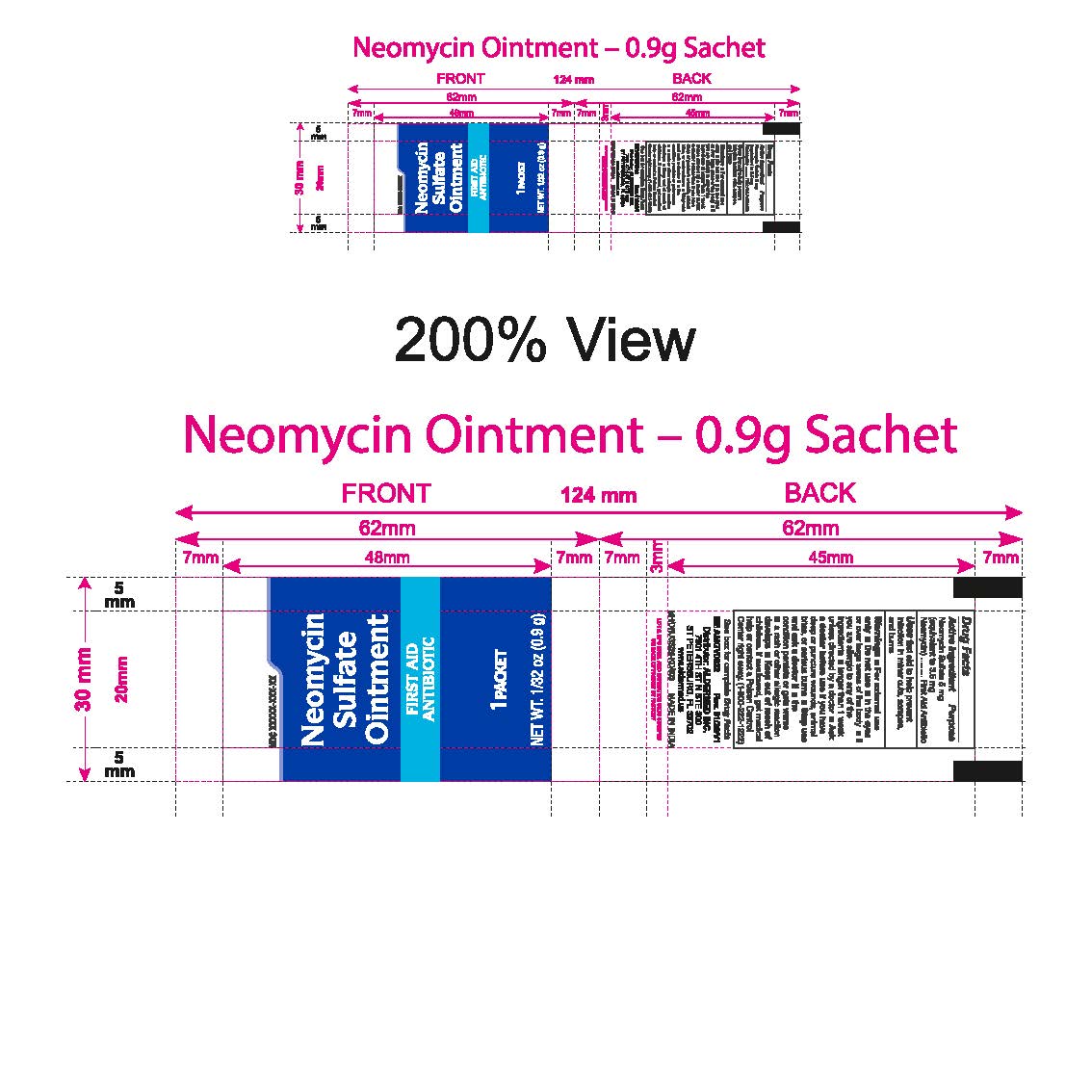 DRUG LABEL: Neomycin Sulfate
NDC: 87236-017 | Form: OINTMENT
Manufacturer: Aldermed Inc.
Category: otc | Type: HUMAN OTC DRUG LABEL
Date: 20260212

ACTIVE INGREDIENTS: NEOMYCIN SULFATE 5 mg/100 g
INACTIVE INGREDIENTS: WHITE PETROLATUM

Neomycin Sulfate Ointment

Active Ingredient

Neomycin Sulfate 5mg (equivalent to 3.5 mg Neomycin)

Purpose

First Aid Antibiotic

Use(s)

■ First aid to help prevent infection in minor cuts, scrapes, and burns

Warnings

For External Use Only

Do not use

■ in the eyes or over large areas of the body

■ if you are allergic to any of the ingredients

■ longer than 1 week unless directed by a doctor

Ask a doctor before use

■ if you have deep or puncture wounds, animal bites, or serious burns

Stop use and ask a doctor if

■ the condition persist or get worse

■ a rash or other allergic reaction develops

Keep out of reach of children

If swallowed, get medical help or contact a Poison Control Center right away.(1-800-222-1222)

Directions

■ clean the affected area

■ apply a small amount of this product (an amount equal to the surface area of the tip of a finger) on the area 1 to 3 times daily

■ may be covered with a sterile bandage

Other Information

• Store at room temperature

• Tamper Evident. Do not use if seal is torn, cut, or opened.

- See sachet or carton for lot number and expiry date

Inactive Ingredients

white petrolatum

Questions?

Call 1-833-605-84-74 9am-5 pm EST M-F